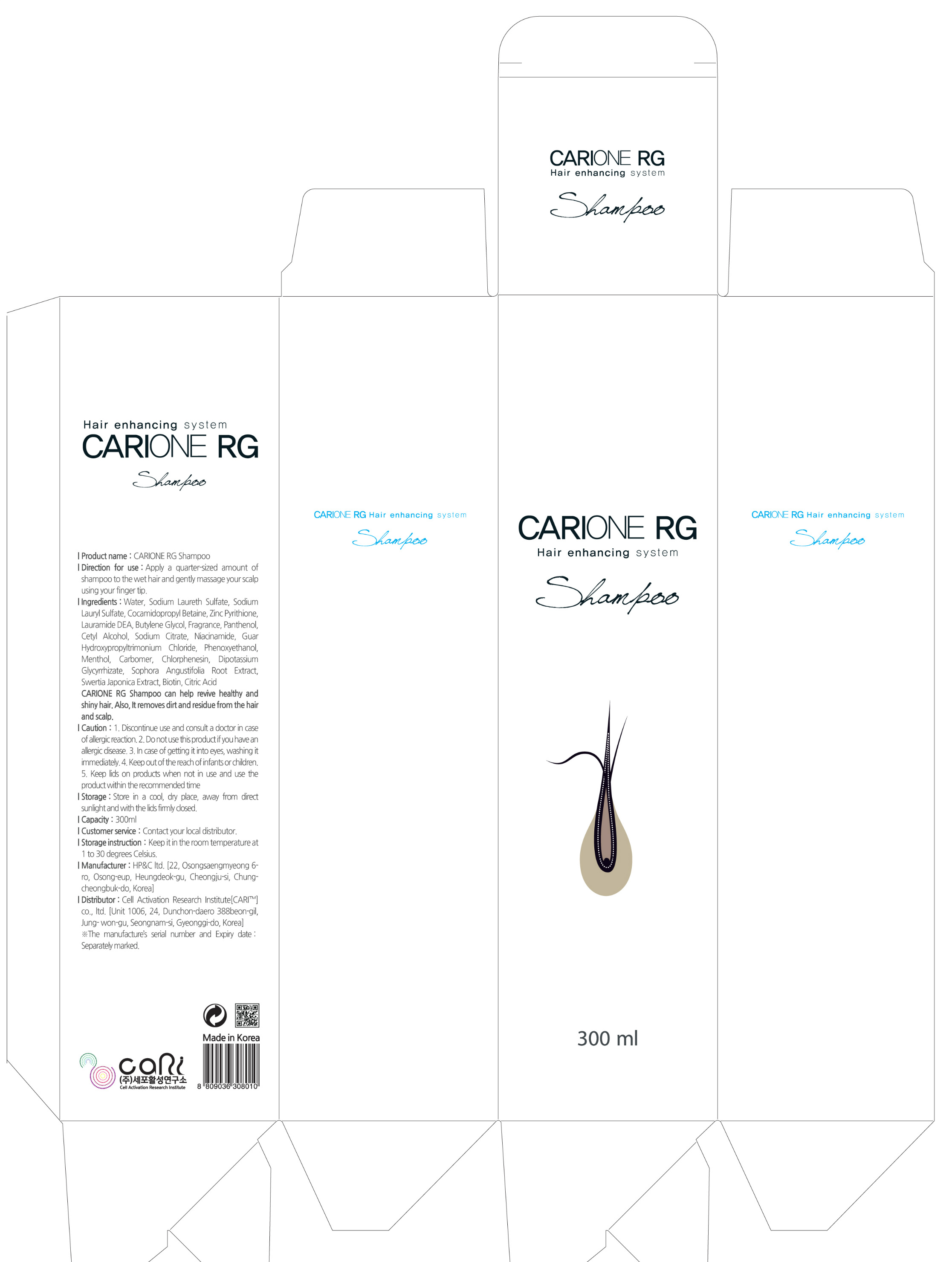 DRUG LABEL: CARIONE RG
NDC: 71039-0001 | Form: SHAMPOO
Manufacturer: Cell Activation Research Institute Co., Ltd
Category: otc | Type: HUMAN OTC DRUG LABEL
Date: 20161023

ACTIVE INGREDIENTS: NIACINAMIDE 0.3 g/100 mL; PANTHENOL 0.5 g/100 mL; PYRITHIONE ZINC 2.1 g/100 mL; BIOTIN 0.06 g/100 mL
INACTIVE INGREDIENTS: WATER

Drug Facts

ACTIVE INGREDIENT

Zinc Pyrithione, Panthenol, Niacinamide, Biotin

INACTIVE INGREDIENT

Water, Sodium Laureth Sulfate, Sodium Lauryl Sulfate, Cocamidopropyl Betaine, Butylene Glycol, etc.

PURPOSE

For hair and scalp care

keep out or reach of the children

INDICATIONS AND USAGE

Apply a quarter-sized amount of shampoo to the wet hair and gently massage your scalp usinng your finger tip.

WARNINGS

1. Discontinue use and consult a doctor in case of allergic reaction.
2. Do not use this product if you have an allergic disease.
3. In case of getting it into eyes, washing it immediately.
4. Keep out of the reach of infants or children.
5. Keep lids on products when not in use and use the product wihin the recommended time.

Storage: Store in a cool, dry place, away from direct sunlight and with the lids firmly close.

DOSAGE AND ADMINISTRATION

For external use only